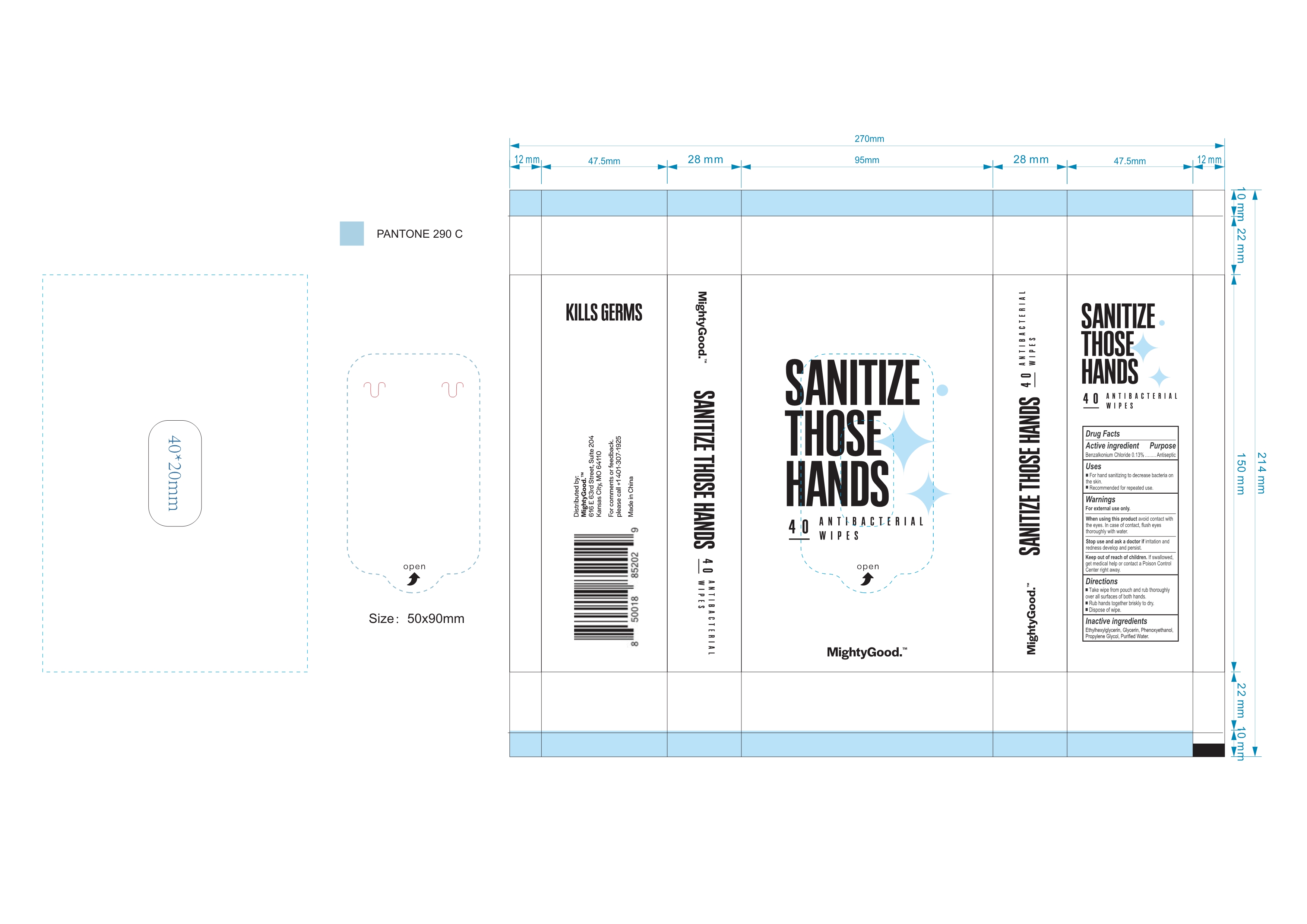 DRUG LABEL: Sanitize Those Hands 40 Antibacterial Wipes
NDC: 42129-019 | Form: CLOTH
Manufacturer: Fustin (Xiamen) Commodity Co., Ltd.
Category: otc | Type: HUMAN OTC DRUG LABEL
Date: 20200821

ACTIVE INGREDIENTS: BENZALKONIUM CHLORIDE 0.13 g/100 1
INACTIVE INGREDIENTS: ETHYLHEXYLGLYCERIN; GLYCERIN; WATER; PHENOXYETHANOL; PROPYLENE GLYCOL

42129-019
Sanitize Those Hands 40 Antibacterial Wipes

Active Ingredient(s)

Benzalkonium Chloride 0.13%

Purpose

Antiseptic

Use

For hand sanitizing to decrease bacteria on the skin.
Recommended for repeated use.

Warnings

For external use only.

When using this product avoid contact with the eyes. In case of contact, flush eyes thoroughly with water.

Stop use and ask a doctor if irritation and redness develop and persist.

Keep out of reach of children. If swallowed, get medical help or contact a Poison Control Center right away.

KEEP OUT OF REACH OF CHILDREN

·Keep out of reach of crildren.lf swallowed get medical help or contact a Poison Control Center right away.

When using this product avoid contact with the eyes. In case of contact, flush eyes thoroughly with water.

Stop use and ask a doctor if irritation and redness develop and persist.

Keep out of reach of children. If swallowed, get medical help or contact a Poison Control Center right away.

Do not use

/

Stop use and ask a doctor if irritation and redness develop and persist.

Directions

Take wipe from pouch and rub thoroughly over all surfaces of both hands.
Rub hands together briskly to dry.
Dispose of wipe.

STORAGE AND HANDLING

/

Inactive ingredients

Ethylhexylglycerin, Glycerin, Phenoxyethanol, Propylene Glycol, Purified Water.